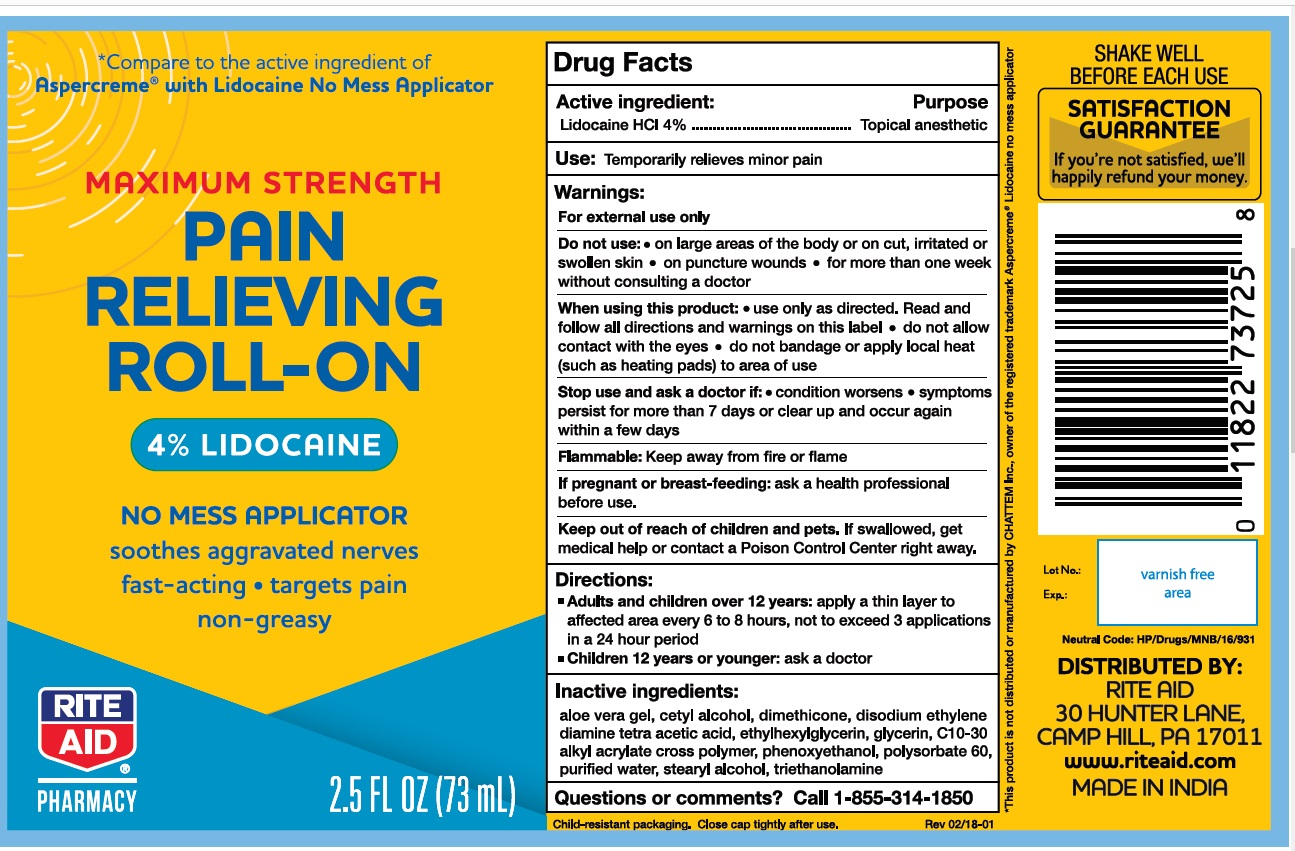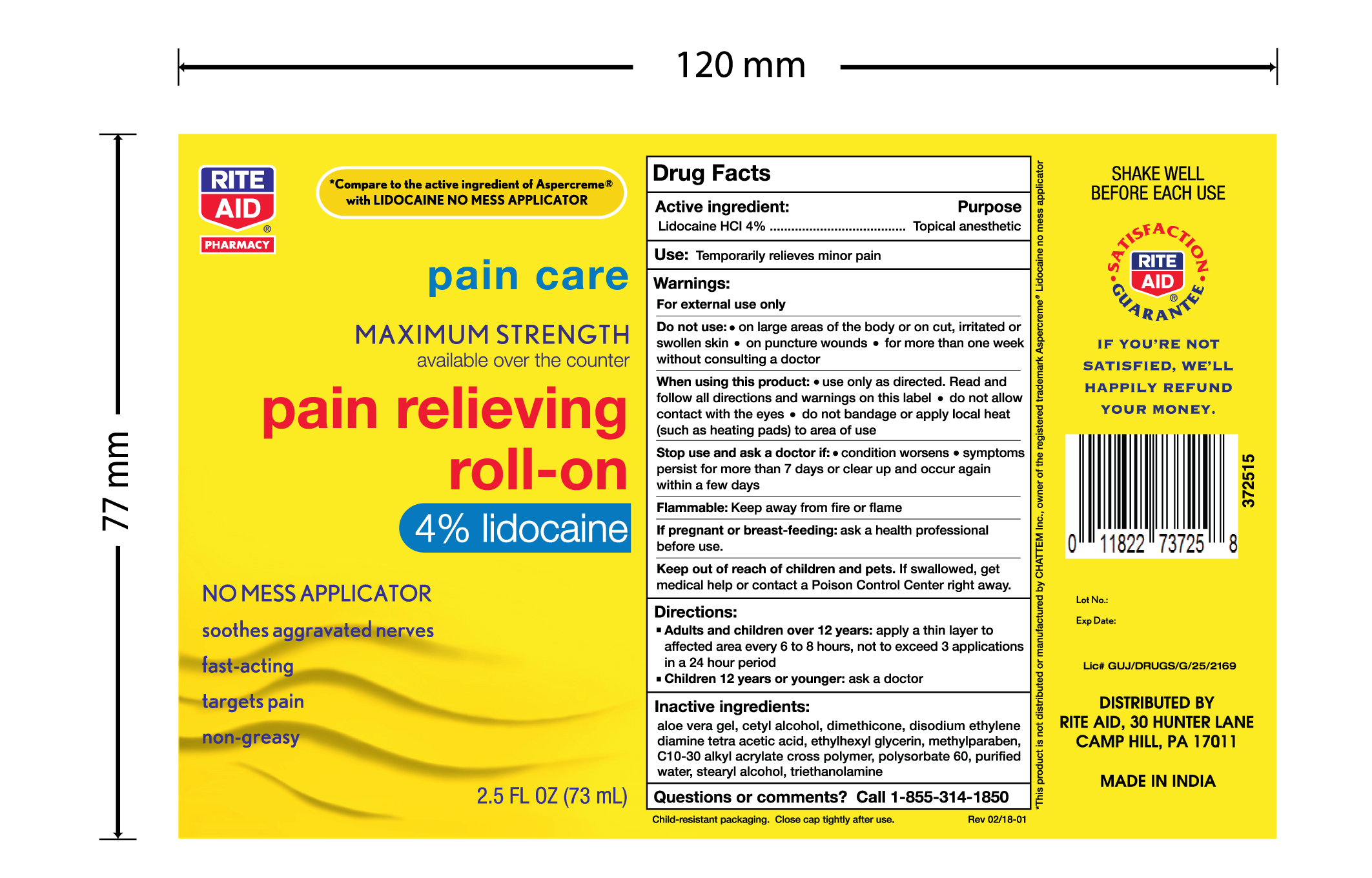 DRUG LABEL: Rite Aid Lidocaine Roll on
NDC: 76168-307 | Form: LIQUID
Manufacturer: Velocity Pharma LLC
Category: otc | Type: HUMAN OTC DRUG LABEL
Date: 20201005

ACTIVE INGREDIENTS: LIDOCAINE HYDROCHLORIDE 4 g/100 mL
INACTIVE INGREDIENTS: ALOE VERA LEAF; GLYCERIN; CETYL ALCOHOL; CETETH-20 PHOSPHATE; CARBOMER INTERPOLYMER TYPE A (55000 CPS); DIMETHICONE; EDETATE DISODIUM ANHYDROUS; ETHYLHEXYLGLYCERIN; PHENOXYETHANOL; TROLAMINE; POLYSORBATE 60; STEARYL ALCOHOL; WATER

Rite Aid Lidocaine Roll on 2.5oz

Drug Facts

Active ingredient

Lidocaine HCl 4%

Purpose

Topical anesthetic

Use

temporarily relieves minor pain

Warnings

For external use only

Do not use

- on large areas of the body or on cut, irritated or swollen skin
- on puncture wounds
- for more than one week without consulting a doctor

When using this product

- use only as directed. Read and follow all directions and warnings on this carton.
- do not allow contact with the eyes
- do not bandage or apply local heat (such as heating pads) to area of use

Stop use and ask a doctor if

- condition worsens
- symptoms persist for more than 7 days or clear up and occur again within a few days

Flammable

- keep away from fire or flame

If pregnant or breast-feeding,

ask a health professional before use.

Keep out of reach of children and pets.

If swallowed, get medical help or contact a Poison

Control Center right away.

Directions

adults and children over 12 years:

- apply a thin layer to affected area every 6 to 8 hours, not to exceed 3 applications in a 24 hour period

children 12 years or younger: ask a doctor

Inactive ingredients

aloe vera gel, cetyl alcohol, dimethicone, disodium EDTA, ethylhexylglycerin, C10-30 alkyl acrylate cross polymer, polysorbate 60, glycerin, triethanolamine, water, stearyl alcohol.

Child-resistant packaging. Close cap tightly after use. Keep carton as it contains important information.